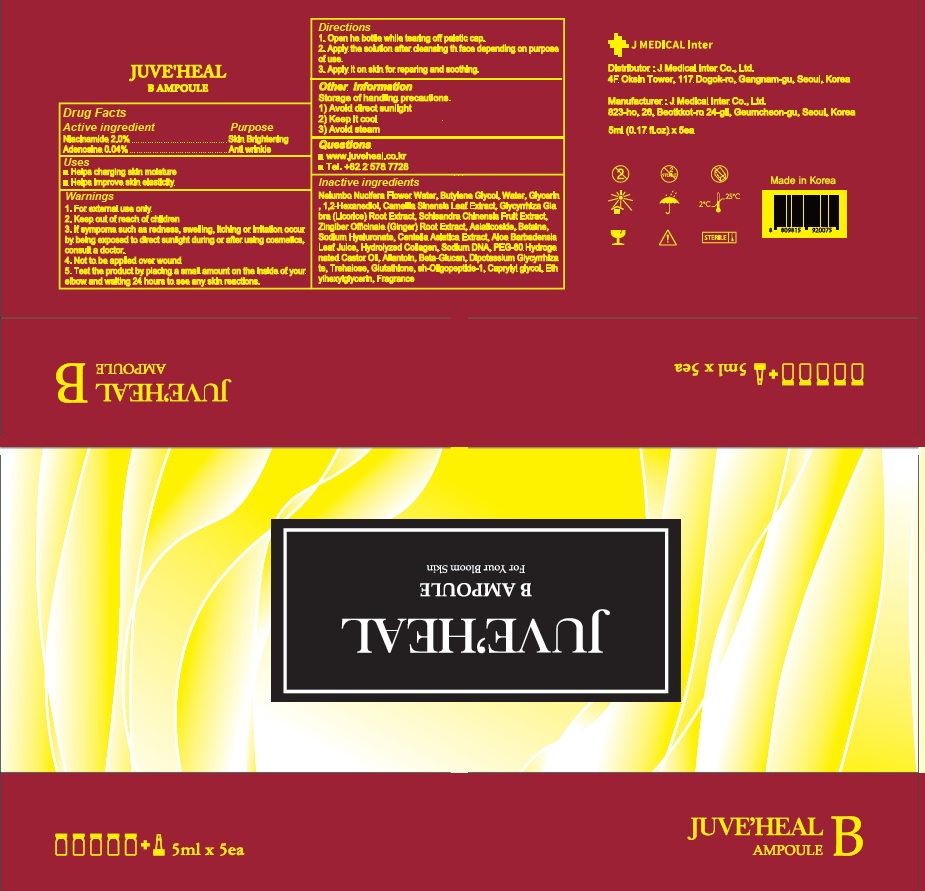 DRUG LABEL: JUVEHEAL B Ampoule
NDC: 81689-020 | Form: LIQUID
Manufacturer: J MEDICAL Inter Co., Ltd.
Category: otc | Type: HUMAN OTC DRUG LABEL
Date: 20210621

ACTIVE INGREDIENTS: Niacinamide 2 g/100 mL; Adenosine 0.04 g/100 mL
INACTIVE INGREDIENTS: NELUMBO NUCIFERA FLOWER OIL; Butylene Glycol; Water

ACTIVE INGREDIENTS

Niacinamide 2.0%
Adenosine 0.04%

INACTIVE INGREDIENTS

Nelumbo Nucifera Flower Water, Butylene Glycol, Water, Glycerin, 1,2-Hexanediol, Camellia Sinensis Leaf Extract, Glycyrrhiza Glabra (Licorice) Root Extract, Schisandra Chinensis Fruit Extract, Zingiber Officinale (Ginger) Root Extract, Asiaticoside, Betaine, Sodium Hyaluronate, Centella Asiatica Extract, Aloe Barbadensis Leaf Juice, Hydrolyzed Collagen, Sodium DNA, PEG-60 Hydrogenated Castor Oil, Allantoin, Beta-Glucan, Dipotassium Glycyrrhizate, Trehalose, Glutathione, sh-Oligopeptide-1, Caprylyl glycol, Ethylhexylglycerin, Fragrance

PURPOSE

Skin Brightening
Anti wrinkle

WARNINGS

1. For external use only
2. Keep out of reach of children
3. If sympoms such as redness, swelling, itching or irritation occur by being exposed to direct sunlight during or after using cosmetics, consult a doctor.
4. Not to be applied over wound
5. Test the product by placing a small amount on the inside of your elbow and waiting 24 hours to see any skin reactions.

KEEP OUT OF REACH OF CHILDREN

Uses

■ Helps charging skin moisture
■ Helps improve skin elasticity

Directions

1. Open he bottle while tearing off palstic cap.
2. Apply the solution after cleansing th face depending on purpose of use.
3. Apply it on skin for reparing and soothing.

Other information

Storage of handling precautions.
1) Avoid direct sunlight
2) Keep it cool
3) Avoid steam

QUESTIONS

■ http://juveheal.co.kr/products.php
■ Tel. +82 2 578 7728